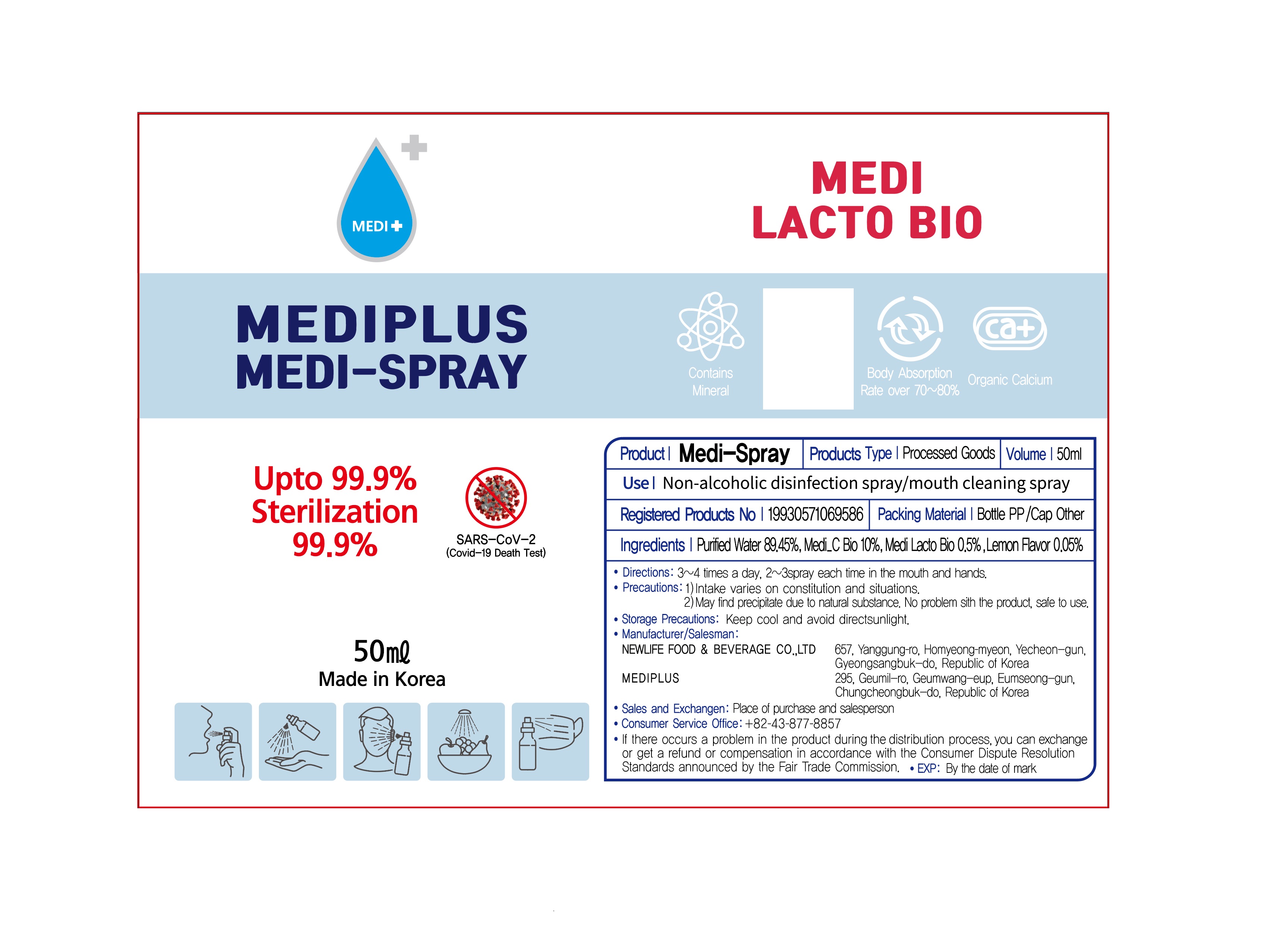 DRUG LABEL: MEDISPRAY
NDC: 82622-0001 | Form: LIQUID
Manufacturer: MEDIPLUS
Category: otc | Type: HUMAN OTC DRUG LABEL
Date: 20220414

ACTIVE INGREDIENTS: OYSTER SHELL CALCIUM CARBONATE, CRUDE 10 g/100 mL
INACTIVE INGREDIENTS: WATER; LEMON

ACTIVE INGREDIENT

Calcined Weathered Sedimentary Coral Powder

INACTIVE INGREDIENT

levan, lemon flavor, water

PURPOSE

hand sanitizing tissue to help reduce bacteria on the skin

keep out of reach of the children

INDICATIONS AND USAGE

pull ouy wipes and sanitize hands when necessary

Do not use

- in children less than 2 months of age

Do not spray directly with your eyes open. If it gets into your eyes and causes irritation, rinse thoroughly with water.

Stop use and ask a doctor if irritation or rash occurs. These may be signs of a serious condition.

Keep out of reach of children.

DOSAGE AND ADMINISTRATION

for external use only